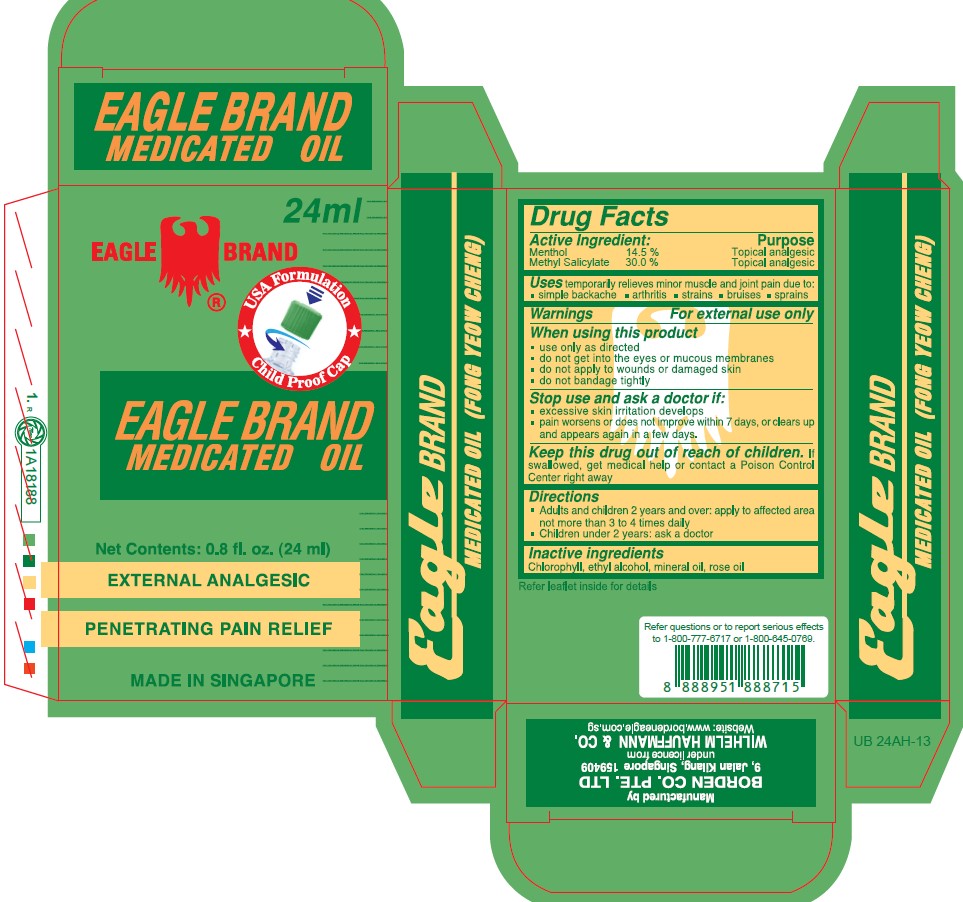 DRUG LABEL: Eagle
NDC: 43405-008 | Form: OIL
Manufacturer: Borden Company (Private) Limited
Category: otc | Type: HUMAN OTC DRUG LABEL
Date: 20250314

ACTIVE INGREDIENTS: METHYL SALICYLATE 30 g/100 mL; MENTHOL 14.5 g/100 mL
INACTIVE INGREDIENTS: CHLOROPHYLL; ALCOHOL; MINERAL OIL; ROSE OIL

Eagle Menthol Mthylslcylte Oil

Active Ingredients

Menthol 14.5%
Methyl Salicylate 30%

Purpose

Topical Analgesic

Topical Analgesic

Uses

temporarily relieves the minor aches and pains of muscle and joints associated with :

■simple backache ■strains ■bruises ■sprains

Warnings

For external use only

When using this product

■use only as directed

■ do not get into eyes or mucous membranes

■ do not apply to wounds or damaged skin

■do not bandage tightly

Stop use and ask a doctor if

■condition worsens or symptoms persist for more than 7 days ■symptoms clear up and occur again within a few days ■excessive skin irritation occurs

Keep this drug out of reach of children

If swallowed, get medical help or contact a Poison Control Center right away.

Directions

■Adults and children 2 years and over: apply to affected area not more than 3 to 4 time daily ■Children under 2 years of age: ask a doctor

Inactive ingredients

Chlorophyll, ethyl alcohol, mineral oil, rose oil